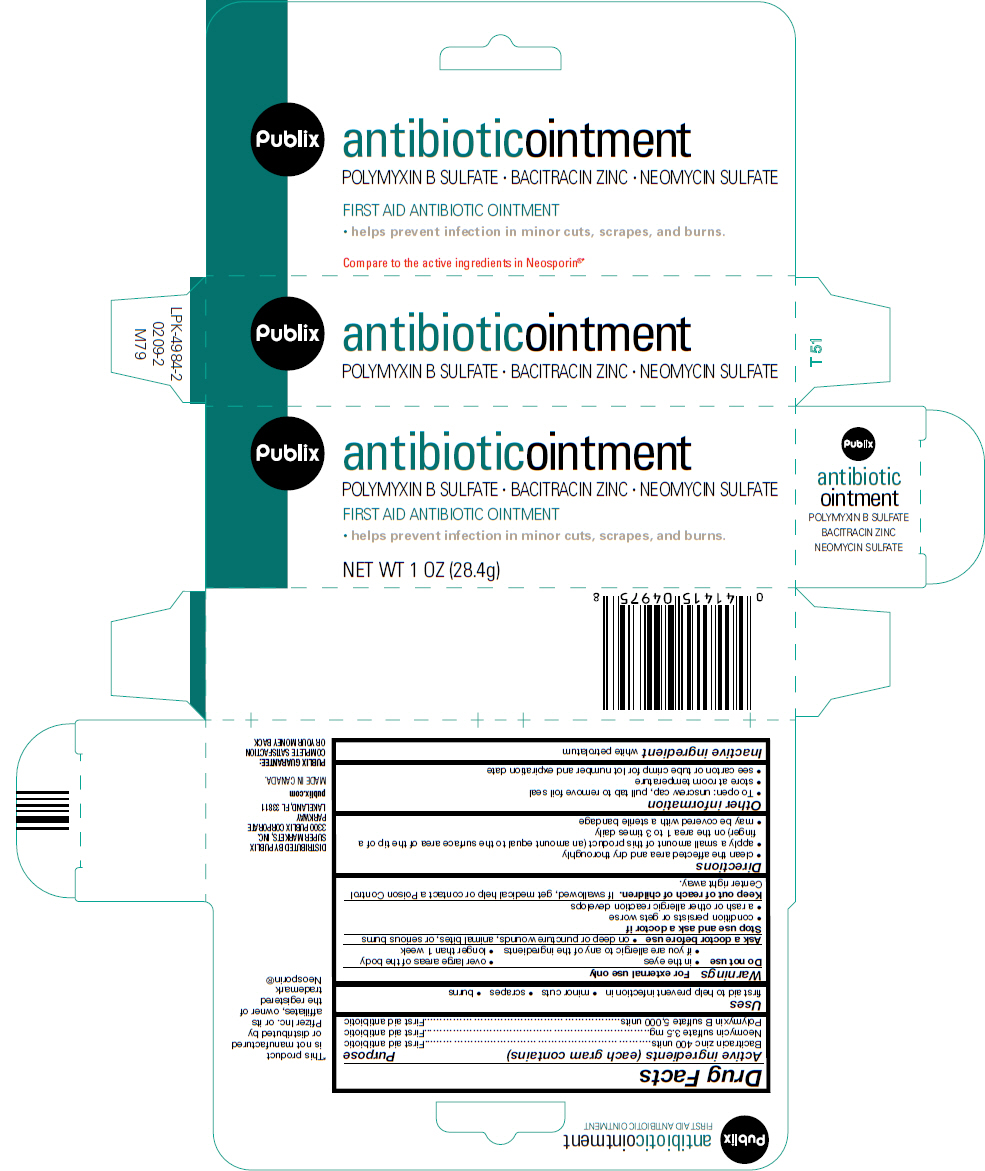 DRUG LABEL: Publix 
NDC: 41415-049 | Form: OINTMENT
Manufacturer: Publix Super Markets Inc
Category: otc | Type: HUMAN OTC DRUG LABEL
Date: 20211214

ACTIVE INGREDIENTS: Bacitracin zinc 400 [iU]/1 g; Neomycin sulfate 3.5 mg/1 g; Polymyxin B sulfate 5000 [iU]/1 g
INACTIVE INGREDIENTS: petrolatum

Publix
antibioticointment

Drug Facts

ACTIVE INGREDIENT

Active ingredients (each gram contains) | Purpose
Bacitracin zinc 400 units | First aid antibiotic
Neomycin sulfate 3.5 mg | First aid antibiotic
Polymyxin B sulfate 5,000 units | First aid antibiotic

Uses

first aid to help prevent infection in

- minor cuts
- scrapes
- burns

Warnings

For external use only

Do not use

- in the eyes
- over large areas of the body
- if you are allergic to any of the ingredients
- longer than 1 week

Ask a doctor before use

- on deep or puncture wounds, animal bites, or serious burns

Stop use and ask a doctor if

- condition persists or gets worse
- a rash or other allergic reaction develops

Keep out of reach of children. If swallowed, get medical help or contact a Poison Control Center right away.

Directions

- clean the affected area and dry thoroughly
- apply a small amount of this product (an amount equal to the surface area of the tip of a finger) on the area 1 to 3 times daily
- may be covered with a sterile bandage

Other information

- To open: unscrew cap, pull tab to remove foil seal
- store at room temperature
- see carton or tube crimp for lot number and expiration date

Inactive ingredient

white petrolatum

DISTRIBUTED BY PUBLIX SUPER MARKETS, INC.
3300 PUBLIX CORPORATE PARKWAY
LAKELAND, FL 33811

PRINCIPAL DISPLAY PANEL - 28.4 g Tube Carton

Publix
antibioticointment

POLYMYXIN B SULFATE • BACITRACIN ZINC • NEOMYCIN SULFATE

FIRST AID ANTIBIOTIC OINTMENT

• helps prevent infection in minor cuts, scrapes, and burns.

NET WT 1 OZ (28.4g)